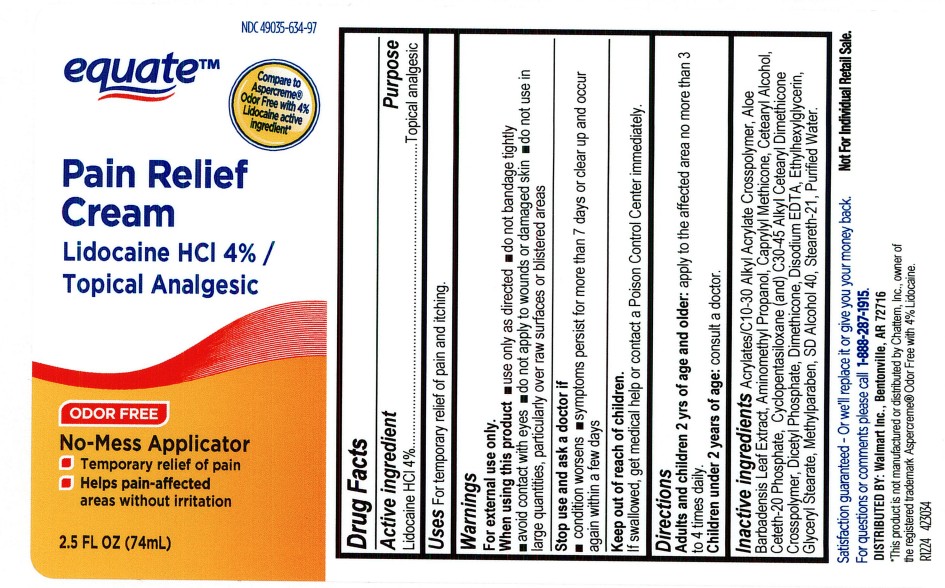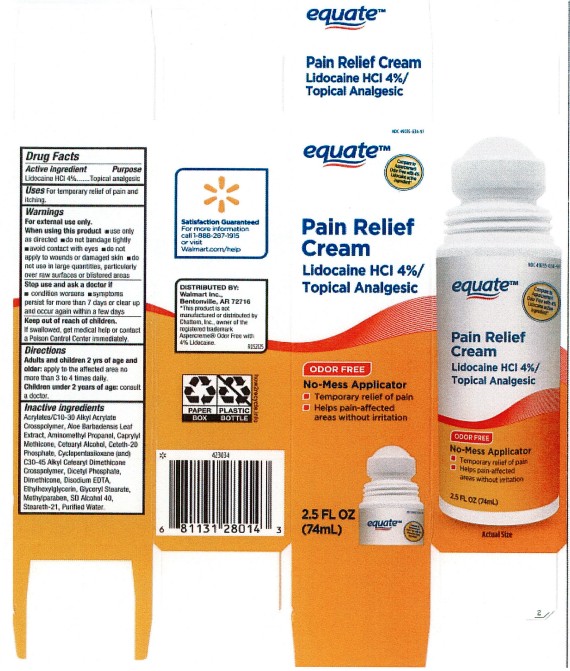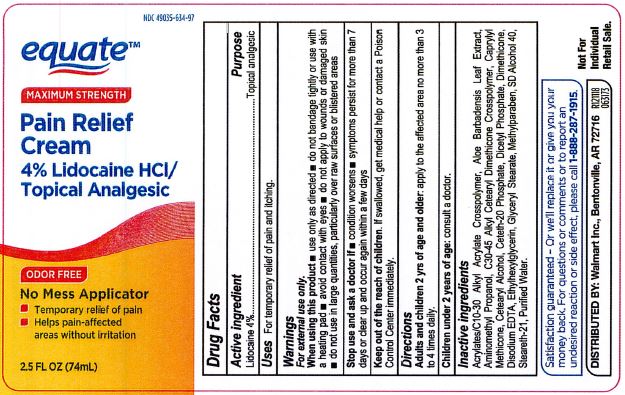 DRUG LABEL: Equate Pain Relief Cream
NDC: 49035-634 | Form: LIQUID
Manufacturer: Walmart, Inc
Category: otc | Type: HUMAN OTC DRUG LABEL
Date: 20251203

ACTIVE INGREDIENTS: LIDOCAINE HYDROCHLORIDE 4 mg/100 mL
INACTIVE INGREDIENTS: ETHYLHEXYLGLYCERIN; METHYLPARABEN; STEARETH-21; WATER; AMINOMETHYLPROPANOL; GLYCERYL STEARATE SE; DISODIUM HEDTA; ALOE VERA LEAF; DIMETHICONE; CAPRYLYL TRISILOXANE; CETEARYL PHOSPHATE; CETETH-20 PHOSPHATE; (C10-C30)ALKYL METHACRYLATE ESTER; C30-45 ALKYL METHICONE; CETOSTEARYL ALCOHOL; ALCOHOL

Equate Pain Relief Cream (Roll On)

DOSAGE AND ADMINISTRATION

Adults and children 2 yrs of age and older: apply to the affected area no more than 3 to 4 times daily.

Children under 2 years of age: consult a doctor.

WARNINGS

For external use only. When using this product:

use only as directed

do not bandage tightly

avoid contact with eyes

do not apply to wounds or damaged skin

do not use in large quantities, particularly over raw surfaces or blistered areas.

INACTIVE INGREDIENT

actylates/C10-C30 Alkyl Acrylate Crosspolymer

Aloe Barbadensis Leaf Etract

Aminoethyl Propanol

C30-C40 Alkyl Cetearyl Dimethicone Crosspolymer

Caprylyl Methicone

Cetearyl Alcohol

Ceteth-20 Phosphate

Dicetyl Phosphate

Dimethicone

Disodium EDTA

Ethylhexylglycerin

Glyceryl Stearate

Methylparaben

SD Alcohol 40

Steareth021

Purified water

INDICATIONS AND USAGE

For temporary relief of pain and itching.

KEEP OUT OF REACH OF CHILDREN

Keep out of the reach of children. If swallowed, get medical help or contact a Poison Control Center immediately.

PURPOSE

Topical Analgesic

ACTIVE INGREDIENT

Lidocaine 4%